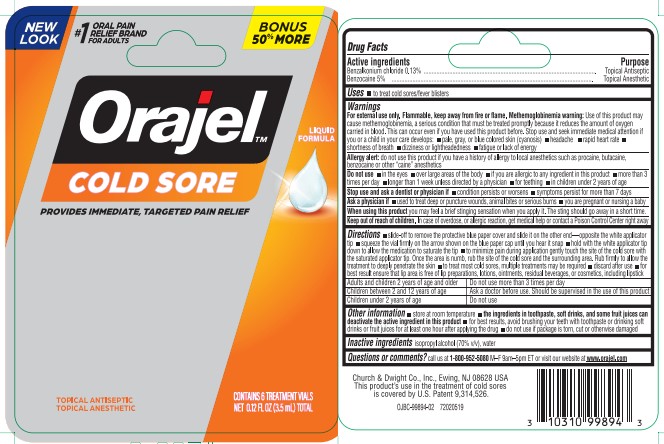 DRUG LABEL: Orajel Cold Sore Touch Free - Single Dose
NDC: 10237-798 | Form: LIQUID
Manufacturer: Church & Dwight Co., Inc.
Category: otc | Type: HUMAN OTC DRUG LABEL
Date: 20251211

ACTIVE INGREDIENTS: BENZALKONIUM CHLORIDE 1.3 mg/1 mL; BENZOCAINE 50 mg/1 mL
INACTIVE INGREDIENTS: WATER; ISOPROPYL ALCOHOL

Orajel Cold Sore Touch Free - Single Dose

Active ingredients

Benzalkonium chloride

Benzocaine

Purpose

Benzalkonium chloride 0.13% ...................................................Topical Antiseptic

Benzocaine 5% .........................................................................Topical Anesthetic

Uses

to treat cold sores/fever blisters

Warnings

For external use only. Flammable, keep away from fire or flame. Methemoglobinemia warning:Use of this product may cause methemoglobinemia, a serious condition that must be treated promptly because it reduces the amount of oxygen carried in blood. This can occur even if you have used this product before. Stop use and seek immediate medical attention if you or a child in your care develops: •pale, gray, or blue colored skin (cyanosis) •headache •rapid heart rate •shortness of breath •dizziness or lightheadedness •fatigue or lack of energy

Allergy alert:do not use this product if you have a history of allergy to local anesthetics such as procaine, butacaine, benzocaine or other "caine" anesthetics

Do not use•in the eyes •over large areas of the body •if you are allergic to any ingredient in this product •more than 3 times per day •longer than 1 week unless directed by a physician •for teething •in children under 2 years of age

Stop use and ask a dentist or physician if•condition persists or worsens •symptoms persist for more than 7 days

ASK DOCTOR

Ask a physician if•used to treat deep or puncture wounds, animal bites or serious burns •you are pregnant or nursing a baby

WHEN USING

When using this productyou may feel a brief stinging when you apply it. The sting should go away in a short time.

Keep out of reach of children.In case of overdose, or allergic reaction, get medical help or contact a Poison Control Center right away

Directions

•slide-off to remove the protective blue paper cover and slide it on the other end - opposite the white applicator tip •squeeze the vial firmly on the arrow shown on the blue paper cap until you hear it snap •hold with the white applicator tip down to allow the medication to saturate the tip •to minimize pain during application gently touch the site of the cold sore with the saturated applicator tip •Once the area is numb, rub the site of the cold sore and the surrounding area. Rub firmly to allow the treatment to deeply penetrate the skin •to treat most cold sores, multiple treatments may be required •discard after use •for best result ensure that lip area is free of lip preparations, lotions, ointments, residual beverages, or cosmetics, including lipstick

Adults and children 2 years of age and older | Do not use more than 3 times per day
Children between 2 and 12 years of age | Ask a doctor before use. Should be supervised in the use of this product
Children under 2 years of age | Do not use

Other information

•store at room temperature • the ingredients in toothpaste, soft drinks, and some fruit juices can deactivate the active ingredient in this product •for best results, avoid brushing your teeth with toothpaste or drinking soft drinks or fruit juices for at least one hour after applying the drug •do not use if package is torn, cut or otherwise damaged

Inactive ingredients

isopropyl alcohol (70% v/v), water

Questions or comments?

call us at 1-800-952-5080M-F 9am-5pm ET or visit our website at www.orajel.com

PACKAGE LABEL

NEW

LOOK

#1 ORAL PAIN

RELIEF BRAND

FOR ADULTS

BONUS

50% MORE

Orajel™

COLD SORE

PROVIDES IMMEDIATE, TARGETED PAIN RELIEF

LIQUID

FORMULA

TOPICAL ANTISEPTIC

TOPICAL ANESTHETIC

CONTAINS 6 TREATMENT VIALS

NET 0.12 FL OZ (3.5 mL) TOTAL